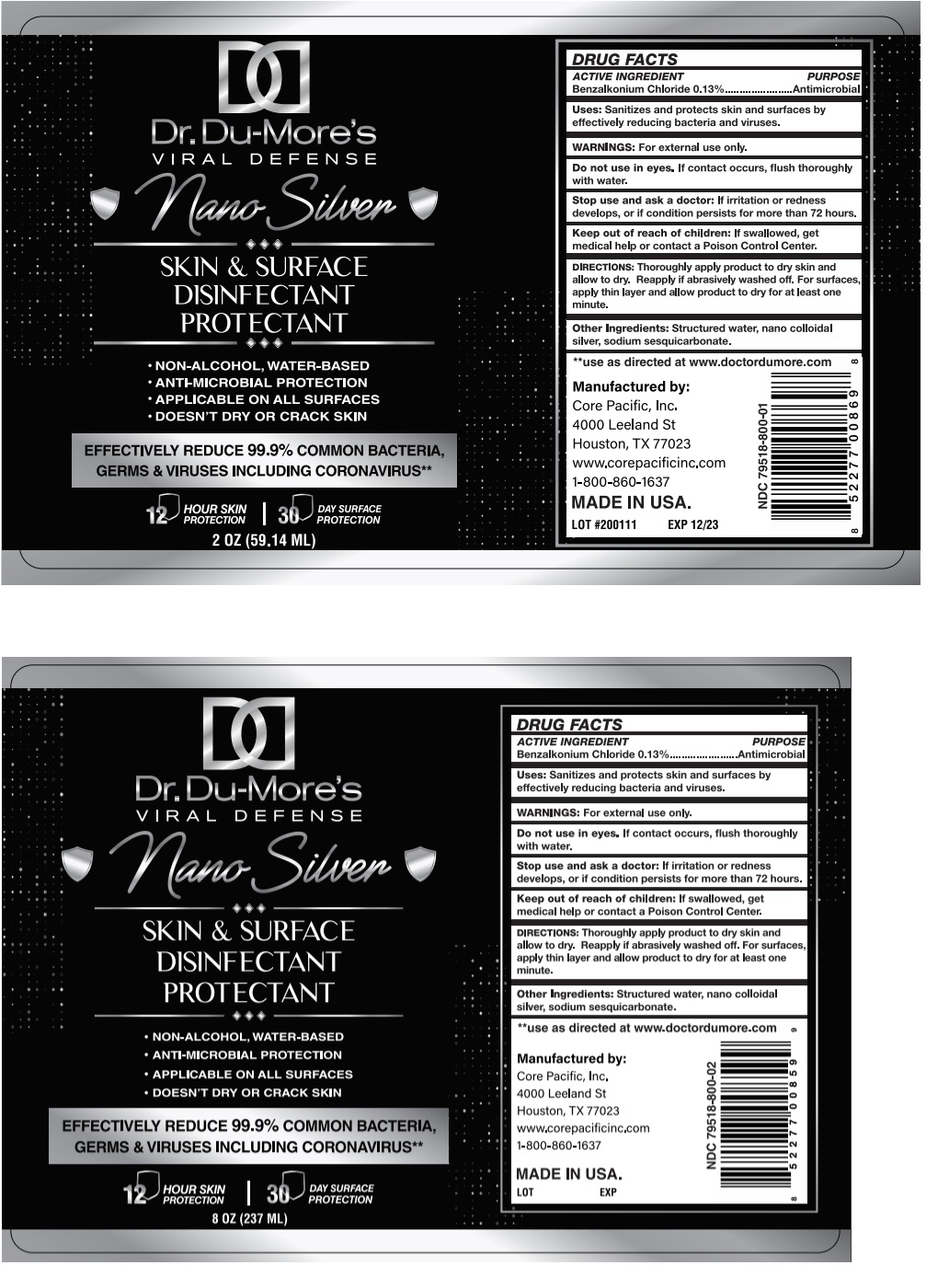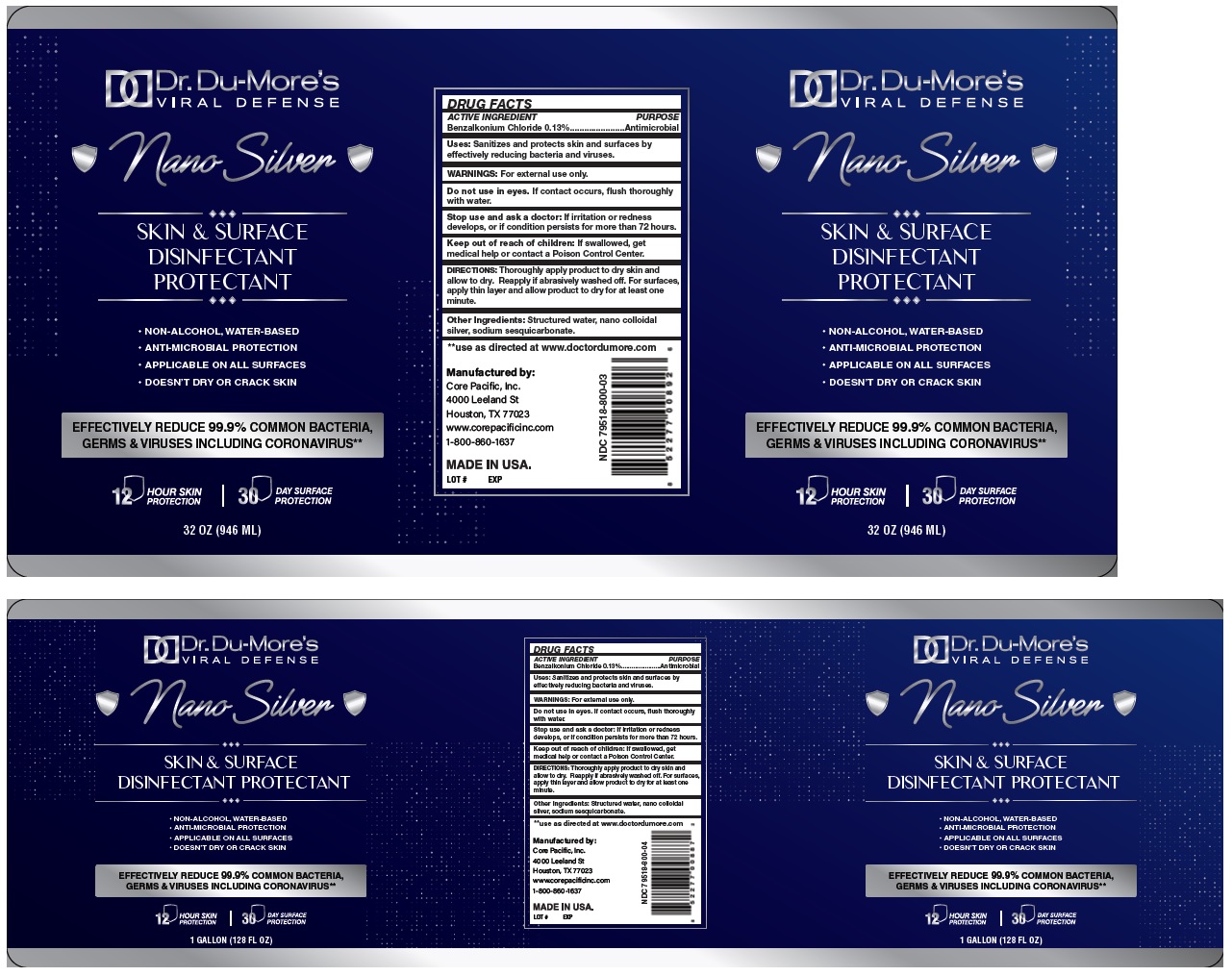 DRUG LABEL: Dr. Du-Mores Viral Defense Nano Silver Skin and Surface Disinfectant Protectant
NDC: 79518-800 | Form: LIQUID
Manufacturer: Core Pacific, Inc.
Category: otc | Type: HUMAN OTC DRUG LABEL
Date: 20201203

ACTIVE INGREDIENTS: BENZALKONIUM CHLORIDE 0.13 g/100 mL
INACTIVE INGREDIENTS: WATER; SILVER; SODIUM SESQUICARBONATE

Dr. Du-More's VIRAL DEFENSE Nano Silver SKIN & SURFACE DISINFECTANT PROTECTANT

ACTIVE INGREDIENT

Benzalkonium Chloride 0.13%

PURPOSE

Antimicrobial

Uses:

Sanitizes and protects skin and surfaces by effectively reducing bacteria and viruses.

WARNINGS:

For external use only.

Do not use in eyes. If contact occurs, flush thoroughly with water.

Stop use and ask a doctor: If irritation or redness develops, or if condition persist for more than 72 hours.

Keep out of reach of children: If swallowed, get medical help or contact a Poison Control Center.

DIRECTIONS:

Thoroughly apply product to dry skin and allow to dry. Reapply if abrasively washed off. For surfaces, apply thin layer and allow products to dry for at least one minute.

Other Ingredients:

Structured water, nano colloidal silver, sodium sesquicarbonate.

• NON-ALCOHOL, WATER-BASED

• ANTI-MICROBIAL PROTECTION

• APPLICABLE ON ALL SURFACES

• DOESN'T DRY OR CRACK SKIN

EFFECTIVELY REDUCE 99.9% COMMON BACTERIA, GERMS & VIRUSES INCLUDING CORONAVIRUS**

12 HOUR SKIN PROTECTION

30 DAY SURFACE PROTECTION

**use as directed at www.doctordumore.com

Manufactured by:

Core Pacific, Inc.

4000 Leeland, St

Houston, TX 77023

www.corepacificinc.com

1-800-860-1637

MADE IN USA.